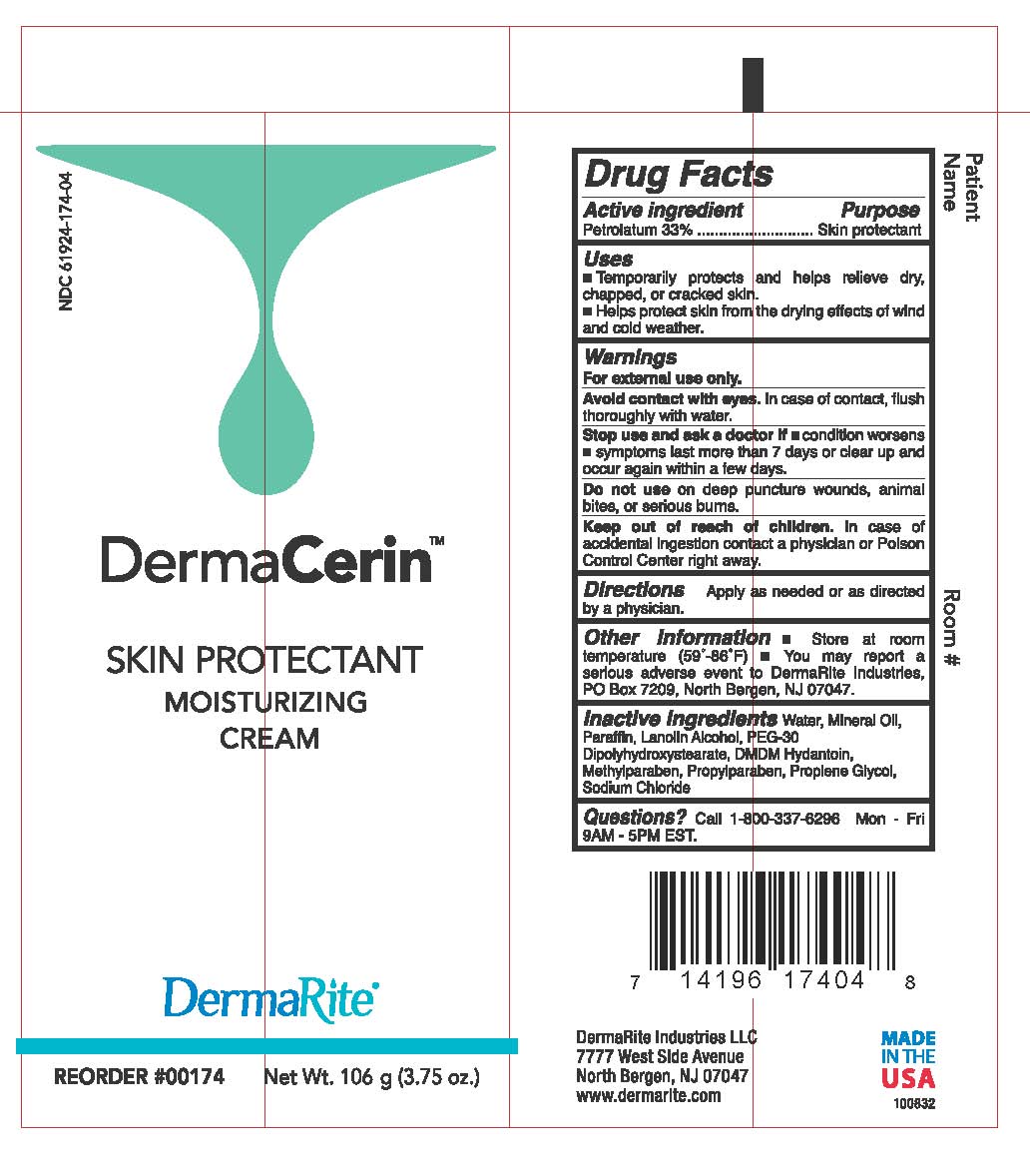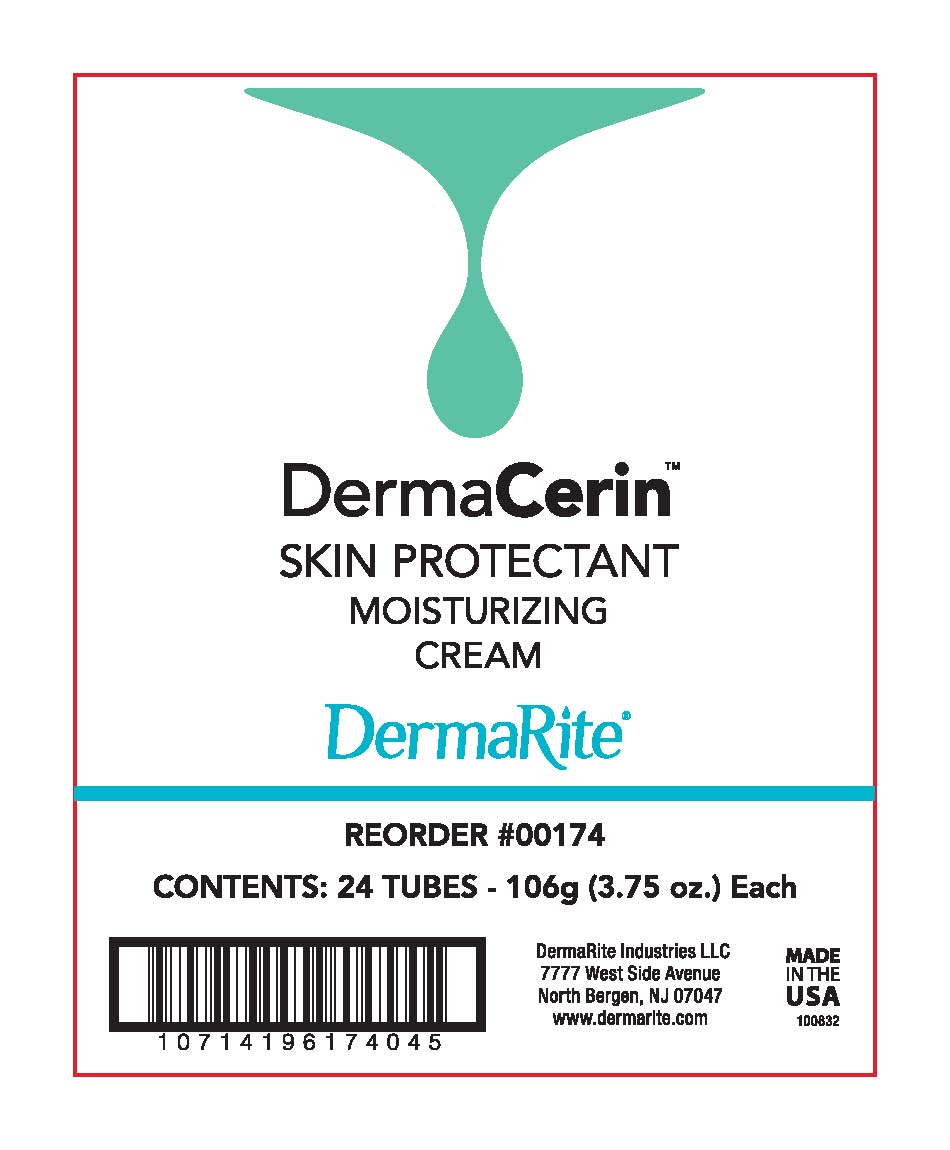 DRUG LABEL: DermaCerin
NDC: 61924-174 | Form: OINTMENT
Manufacturer: DermaRite Industries, LLC
Category: otc | Type: HUMAN OTC DRUG LABEL
Date: 20241205

ACTIVE INGREDIENTS: PETROLATUM 33 g/100 g
INACTIVE INGREDIENTS: PARAFFIN; PROPYLENE GLYCOL 2-(2-METHYLBUTYRATE); WATER; SODIUM CHLORIDE; PROPYLPARABEN; LANOLIN ALCOHOLS; MINERAL OIL; DMDM HYDANTOIN; METHYLPARABEN; PEG-30 DIPOLYHYDROXYSTEARATE

DermaCerin

Active Ingredient:

Petrolatum 33%

Purpose:

Skin Protectant

Uses:

- Temporarily protects and helps relieve dry, chapped, or cracked skin.
- Helps protect skin from the drying effects of wind and cold weather.

Warnings:

For external use only.

Avoid contact with eyes. In case of contact, flush thoroughly with water

Warnings:

Stop and ask a doctor if

- condition worsens
- symptoms last more than 7 days or clear up and occur again within a few days.

Warnings:

Do not use on deep or puncture wounds, animal bites, or serious wounds.

Warnings:

Keep out of reach of children.

In case of accidental ingestion contact a Physician or Poison Control Center right away.

Directions:

Apply as needed or as directed by a physician.

Other Information:

- Store at room temperature (59º- 86ºF)
- You may report a serious adverse event to DermaRite Industries, PO Box 7209, North Bergen, NJ 07047.

Inactive ingredients:

Water, Mineral Oil, Paraffin, Lanolin Alcohol, PEG-30 Dipolhydroxystearate, DMDM Hydantoin, Methylparaben, Propylparaben, Propylene Glycol, Sodium Chloride

Questions?

Call 800-337-6296 Mon - Fri 9AM - 5PM EST.